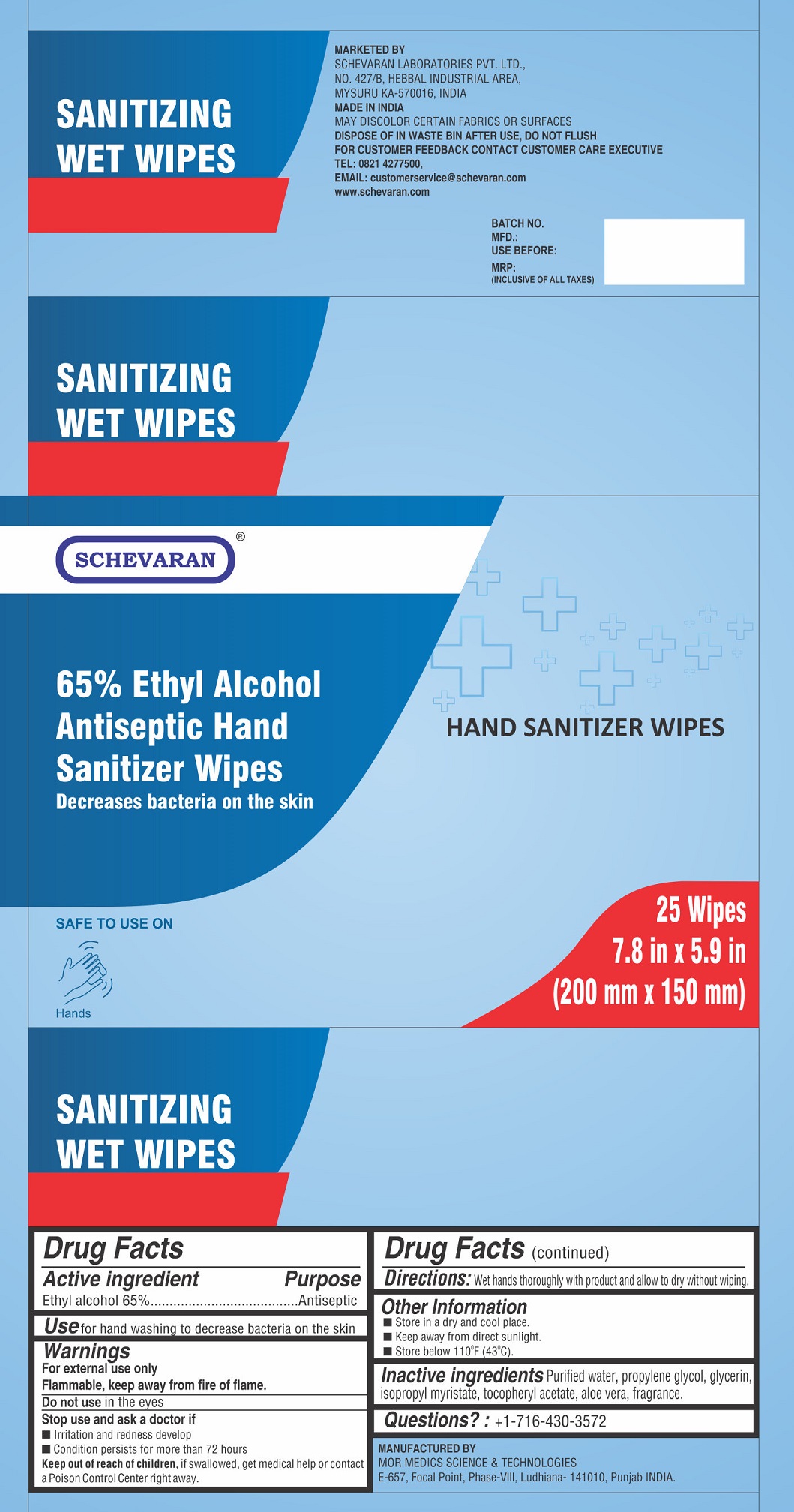 DRUG LABEL: 65 Ethyl Alcohol Antiseptic Hand Sanitizer Wipes
NDC: 82444-002 | Form: CLOTH
Manufacturer: SCHEVARAN LABORATORIES PRIVATE LIMITED
Category: otc | Type: HUMAN OTC DRUG LABEL
Date: 20220310

ACTIVE INGREDIENTS: ALCOHOL 65 mL/100 mL
INACTIVE INGREDIENTS: WATER; PROPYLENE GLYCOL; GLYCERIN; ISOPROPYL MYRISTATE; .ALPHA.-TOCOPHEROL ACETATE; ALOE VERA LEAF

65% Ethyl Alcohol Antiseptic Hand Sanitizer Wipes

Active ingredient

Ethyl alcohol 65%

Purpose

Antiseptic

Use

for hand washing to decrease bacteria on the skin

Warnings

For external use only

Flammable, keep away from fire or flame.

Do not use

in the eyes

Stop use and ask a doctor if

- Irritation and redness develop
- Condition persists for more than 72 hours

Keep out of reach of children,

if swallowed, get medical help or contact a Poison Control Center right away.

Directions:

Wet hands thoroughly with product and allow to dry without wiping.

Other Information

- Store in a dry and cool place.
- Keep away from direct sunlight.
- Store below 110°F (43°C).

Inactive ingredients

Purified water, propylene glycol, glycerin, isopropyl myristate, tocopheryl acetate, aloe vera, fragrance.

Questions?:

+1-716-430-3572